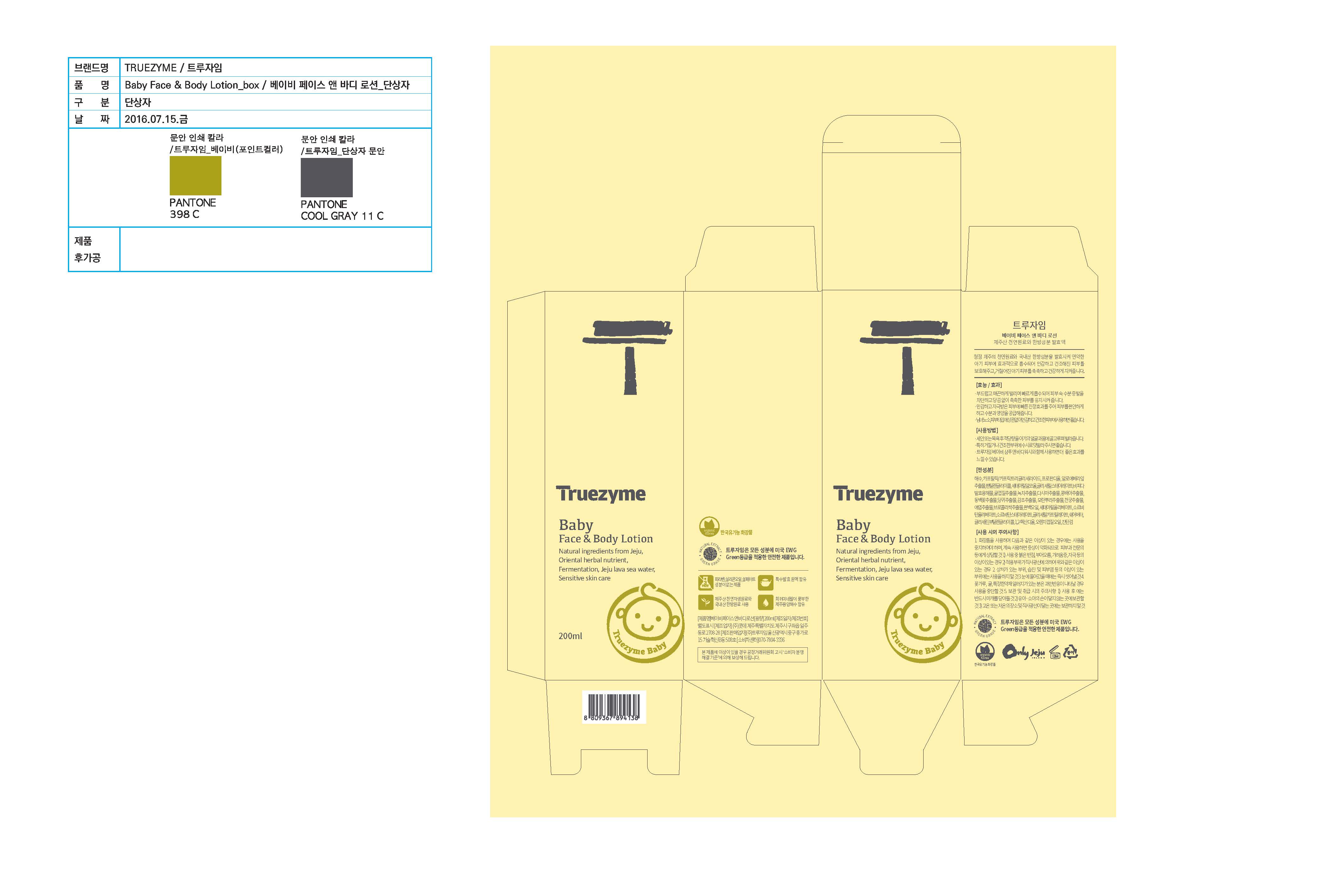 DRUG LABEL: Truezyme Baby Face and Body
NDC: 71076-0001 | Form: LOTION
Manufacturer: Truezyme Co., Ltd.
Category: otc | Type: HUMAN OTC DRUG LABEL
Date: 20161114

ACTIVE INGREDIENTS: GLYCERIN 0.008 g/100 mL
INACTIVE INGREDIENTS: SHEA BUTTER; ALOE VERA LEAF; MEDIUM-CHAIN TRIGLYCERIDES

Drug Facts

Active ingredient

Glycerin

Purpose

Skin protectant

DOSAGE AND ADMINISTRATION

For external use only

INDICATIONS AND USAGE

- Apply to baby's face and body evenly after a bath or washing.
- Apply to dry, rough-textured area repeatedly.
- Use with Truezyme Baby Shampoo & Body Wash for better results.

Inactive ingredients:

Sea Water, Caprylic/Capric Triglyceride, Propanediol, Aloe Barbadensis Leaf Extract, Butyrospermum Parkii (Shea) Butter, etc.

Keep out of reach of children.

WARNINGS

1. Stop using the product if there are any of the following abnormal symptoms appearing after use and consult with your dermatologist as continued use can worsen the symptoms.

1) If there are red spots, swelling, itchiness, or irritation

2) If the above symptoms appear around the skin to which the product has been applied after being exposed to direct sunlight.

2. Do not apply the product to any parts of the skin with wound, eczema, or dermatitis.

3. If it gets into eye, wash the eye with clean water immediately.

4. Those who are allergic to certain medicinal herb, such as pollen and tangerine, must stop using the product if they experience hypersensitivity.

5. Precautions on storage and handling

1) Make sure to close the cap after use.

2) Keep out of the reach of children.

3) Do not keep the product in a hot or cold place or a place getting direct sunlight.